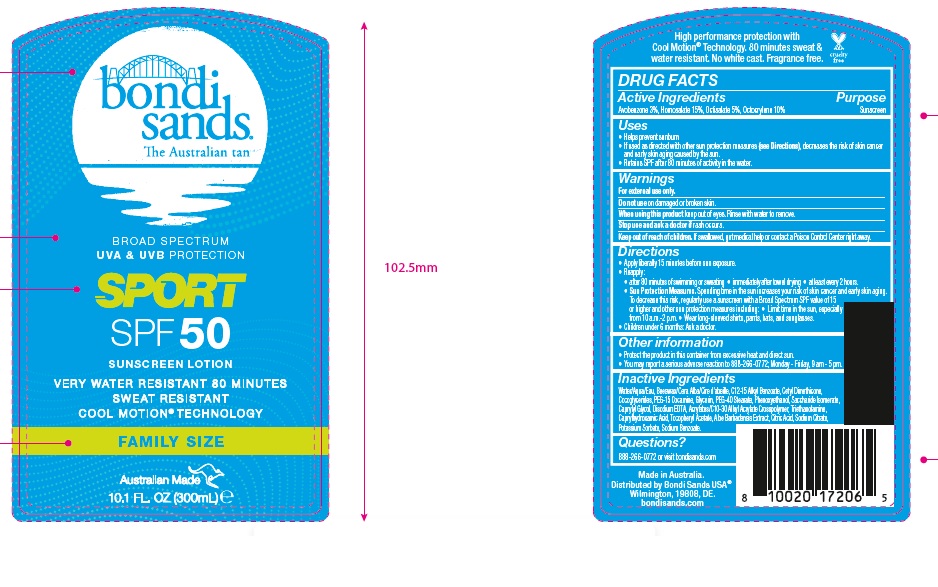 DRUG LABEL: Bondi Sands Sport SPF 50 Sunscreen
NDC: 79950-015 | Form: LOTION
Manufacturer: BONDI SANDS (USA) INC.
Category: otc | Type: HUMAN OTC DRUG LABEL
Date: 20241106

ACTIVE INGREDIENTS: AVOBENZONE 30 mg/1 mL; OCTISALATE 50 mg/1 mL; OCTOCRYLENE 100 mg/1 mL; HOMOSALATE 150 mg/1 mL
INACTIVE INGREDIENTS: POTASSIUM SORBATE; SODIUM BENZOATE; SODIUM CITRATE; YELLOW WAX; PEG-15 COCAMINE; PHENOXYETHANOL; SACCHARIDE ISOMERATE; CAPRYLYL GLYCOL; COCO-GLYCERIDES; .ALPHA.-TOCOPHEROL ACETATE; GLYCERIN; EDETATE DISODIUM; TROLAMINE; CAPRYLHYDROXAMIC ACID; ALOE VERA WHOLE; CITRIC ACID MONOHYDRATE; PEG-40 STEARATE; WATER; ALKYL (C12-15) BENZOATE; CETYL DIMETHICONE 45; CARBOMER COPOLYMER TYPE B (ALLYL PENTAERYTHRITOL CROSSLINKED)

Bondi Sands Sport SPF 50 Sunscreen

Active Ingredients

Avobenzone 3%, Homosalate 15%, Octisalate 5%, Octocrylene 10%

Purpose

Sunscreen

Uses

- Helps prevent sunburn
- If used as directed with other sun protection measures (see Directions), decreases the risk of skin cancer and early skin aging caused by the sun.
- Retains SPF after 80 minutes of activity in the water.

Warnings

For external use only.

Do not use

on damaged or broken skin.

When using this product

keep out of eyes. Rinse with water to remove

Stop use and ask a doctor

if rash occurs

Keep out of reach of children.

If swallowed, get medical help or contact a Poison Control Center right away.

Directions

- Apply liberally 15 minutes before sun exposure.
- Reapply:
- after 80 minutes of swimming or sweating
- immediately after towel drying
- at least every 2 hours.
- Sun Protection Measures. Spending time in the sun increases your risk of skin cancer and early skin aging. To decrease this risk, regularly use a sunscreen with a Broad Spectrum SPF value of 15 or higher and other sun protection measures including:
- Limit time in the sun, especially from 10 a.m.- 2 p.m.
- Wear long sleeved shirts, pants, hats, and sunglasses.
- Children under 6 months: Ask a doctor.

Other information

- Protect the product in this container from excessive heat and direct sun.
- You may report a serious adverse reaction to 888-266-0772; Monday – Friday, 9 am – 5 pm.

Inactive Ingredients

Water/Aqua/Eau, Beeswax/Cera Alba/Cire d'abeille, C12-15 Alkyl Benzoate, Cetyl Dimethicone, Cocoglycerides, PEG-15 Cocamine, Glycerin, PEG-40 Stearate, Phenoxyethanol, Saccharide Isomerate, Caprylyl Glycol, Disodium EDTA, Acrylates/C10-30 Alkyl Acrylate Crosspolymer, Triethanolamine, Caprylhydroxamic Acid, Tocopheryl Acetate, Aloe Barbadensis Extract, Citric Acid, Sodium Citrate, Potassium Sorbate, Sodium Benzoate.

Questions?

888-266-0772 or visit bondisands.com

Company Information

Made in Australia.

Distributed by Bondi Sands USA

Wilmington, 19808, DE.

bondisands.com